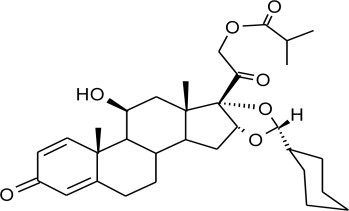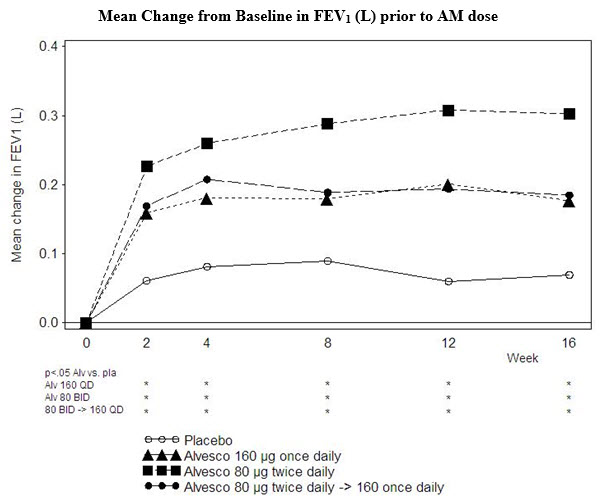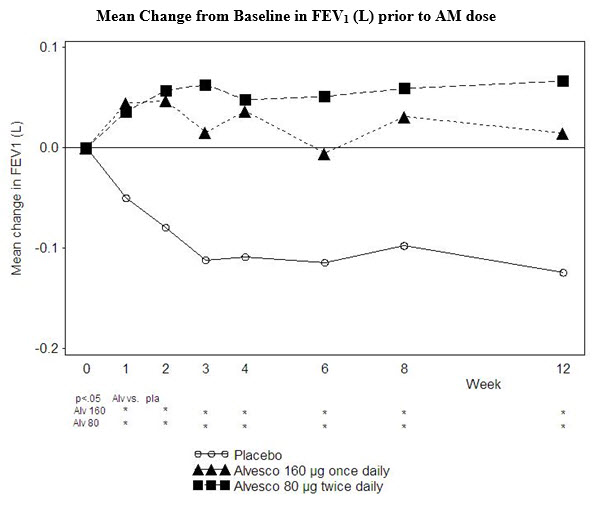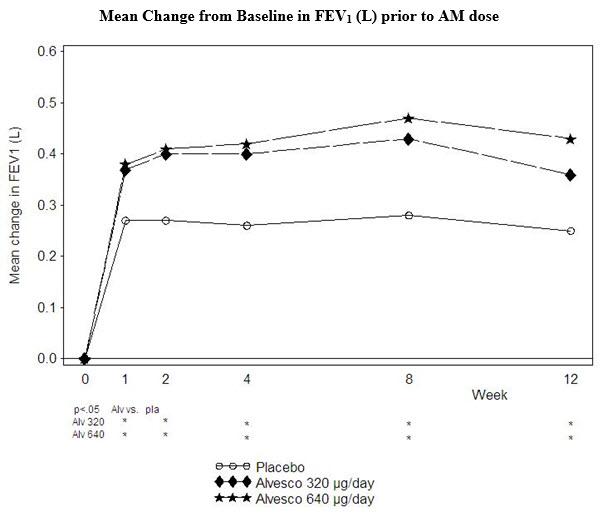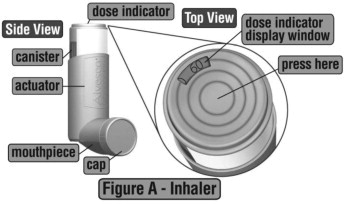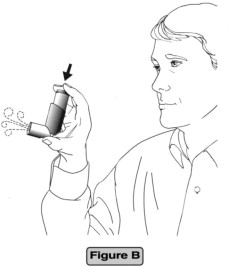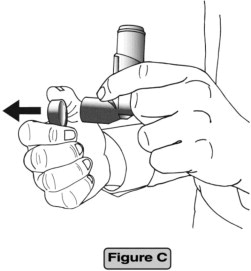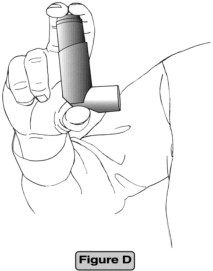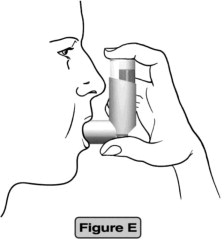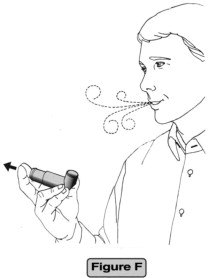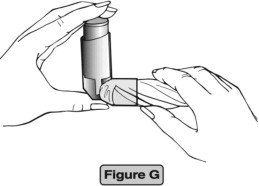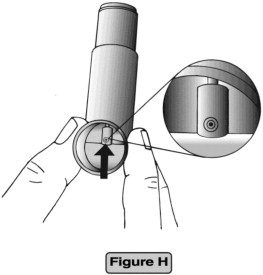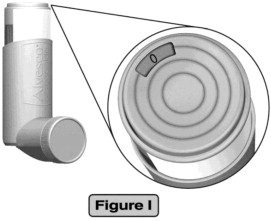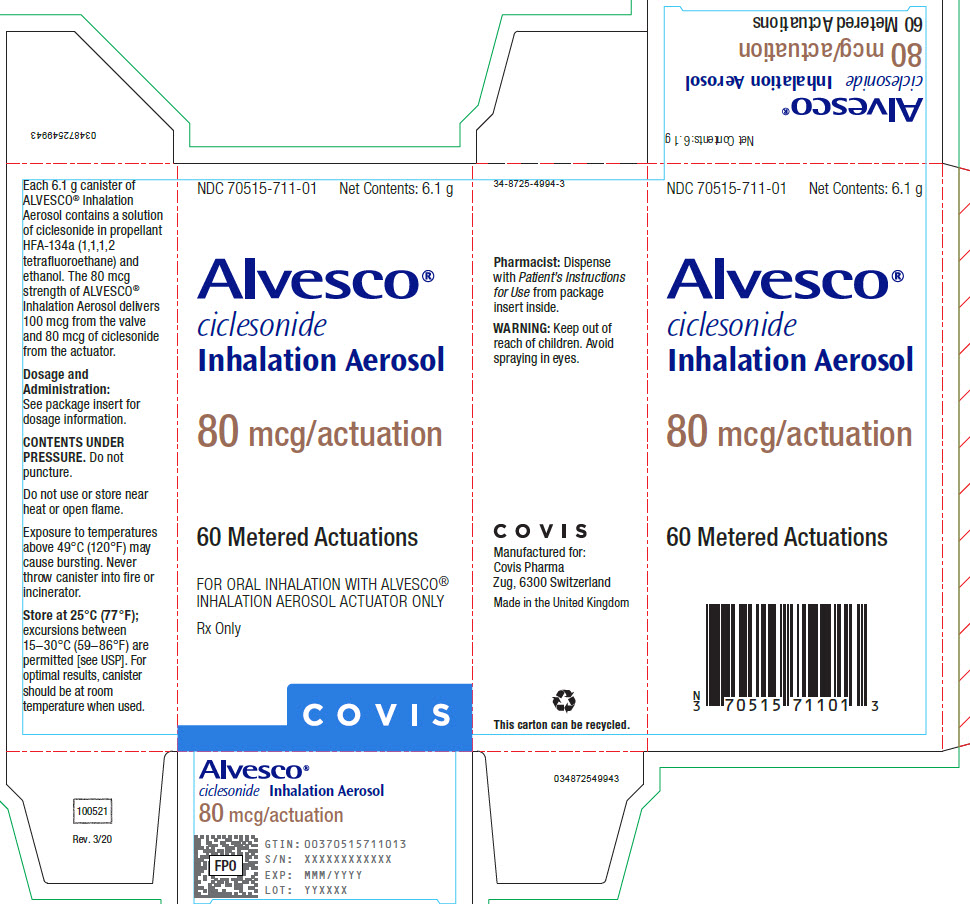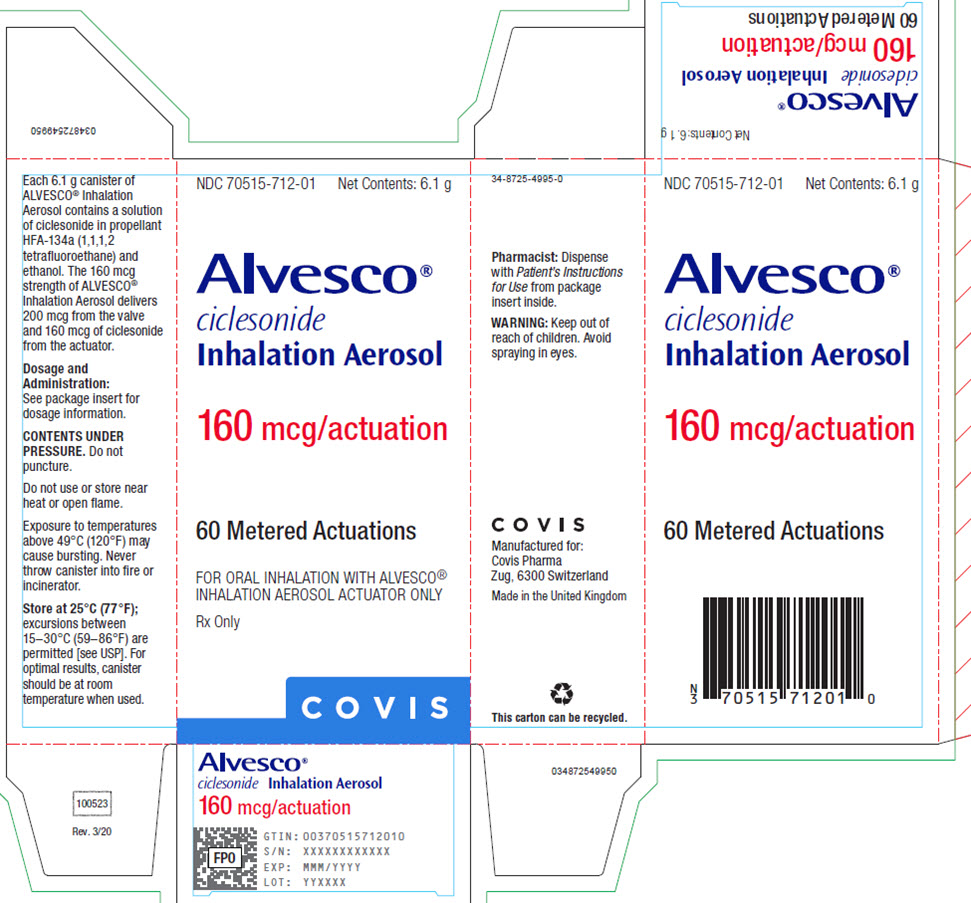 DRUG LABEL: Alvesco
NDC: 70515-711 | Form: AEROSOL, METERED
Manufacturer: Covis Pharma US, Inc
Category: prescription | Type: HUMAN PRESCRIPTION DRUG LABEL
Date: 20250228

ACTIVE INGREDIENTS: CICLESONIDE 80 ug/1 1
INACTIVE INGREDIENTS: NORFLURANE; ALCOHOL

HIGHLIGHTS OF PRESCRIBING INFORMATION

These highlights do not include all the information needed to use ALVESCO®safely and effectively. See full prescribing information for ALVESCO®.
ALVESCO®(ciclesonide) inhalation aerosol, for oral inhalation use
Initial U.S. Approval: 2006

1 INDICATIONS AND USAGE

ALVESCO is an inhaled corticosteroid indicated for maintenance treatment of asthma as prophylactic therapy in adult and pediatric patients 12 years of age and older. (1)

Limitations of Use:

ALVESCO is not indicated for the relief of acute bronchospasm or in pediatric patients less than 12 years of age. (1)

2 DOSAGE AND ADMINISTRATION

- For oral inhalation only. (2)
- Prime ALVESCO before first use or when inhaler not used for more than 10 days. (2)

Previous Therapy | Recommended Starting Dose | Highest Recommended Dose
Patients ≥ 12 years who received bronchodilators alone | 80 mcg twice daily | 160 mcg twice daily
Patients ≥ 12 years who received inhaled corticosteroids | 80 mcg twice daily | 320 mcg twice daily
Patients ≥ 12 years who received oral corticosteroids^1 | 320 mcg twice daily | 320 mcg twice daily
^1Prednisone should be reduced gradually, no faster than 2.5 mg/day on a weekly basis, beginning after at least 1 week of therapy with ALVESCO. Patients should be carefully monitored for signs of asthma instability, including monitoring of serial objective measures of airflow, and for signs of adrenal insufficiency during steroid taper and following discontinuation of oral corticosteroid therapy [see Warnings and Precautions (5.1)] .

3 DOSAGE FORMS AND STRENGTHS

Inhalation aerosol: 80 mcg per actuation or 160 mcg per actuation (3)

4 CONTRAINDICATIONS

- Patients with status asthmaticus or other acute episodes of asthma where intensive measures are required. (4)
- Patients with a known hypersensitivity to ciclesonide or any of the ingredients of ALVESCO. (4)

5 WARNINGS AND PRECAUTIONS

- Candida albicansinfection of the mouth and pharynx. Monitor patients periodically for signs of adverse effects on the oral cavity. Advise patients to rinse mouth following inhalation. (5.1)
- Potential worsening of existing tuberculosis: fungal, bacterial, viral, or parasitic infection; or ocular herpes simplex. More serious or even fatal course of chickenpox or measles in susceptible patients. Use caution in patients with above because of the potential for worsening of these infections. (5.3)
- Risk of impaired adrenal function when transferring from oral steroids to inhaled corticosteroids. Taper patients slowly from systemic corticosteroids if transferring to ALVESCO. (5.4)
- Hypercorticism, suppression of hypothalamic-pituitary-adrenal (HPA) function with very high dosages or at the regular dosage in susceptible individuals. If such changes occur, discontinue ALVESCO slowly (5.5)
- Suppression of growth in children. Monitor growth routinely in pediatric patients receiving ALVESCO. (5.7)
- Development of glaucoma, increased intraocular pressure and posterior subcapsular cataracts. Monitor patients with a change in vision or with a history of increased intraocular pressure, glaucoma, and/or cataracts closely. (5.8)

6 ADVERSE REACTIONS

Most common adverse reactions (≥ 3%) are headache, nasopharyngitis, sinusitis, pharyngolaryngeal pain, upper respiratory infection, arthralgia, nasal congestion, pain in extremity and back pain. (6)

Other adverse reactions have been reported. (6)

To report SUSPECTED ADVERSE REACTIONS, contact Covis Pharma at 1-877-411-2510 or FDA at 1-800-FDA-1088 or www.fda.gov/medwatch.

FULL PRESCRIBING INFORMATION

1 INDICATIONS AND USAGE

ALVESCO is indicated for the maintenance treatment of asthma as prophylactic therapy in adult and pediatric patients 12 years of age and older.

Limitations of Use:

ALVESCO is not indicated for the relief of acute bronchospasm.

ALVESCO is not indicated for children under 12 years of age.

2 DOSAGE AND ADMINISTRATION

2.1 Administration Information

- Administer ALVESCO by the orally inhaled route.
- After administration, rinse the mouth with water and spit out without swallowing to help reduce the risk of oropharyngeal candidiasis [see Warnings and Precautions (5.1)] .

Priming

Prime ALVESCO before using for the first time by actuating 3 times prior to using the first dose from a new canister or when the inhaler has not been used for more than 10 days.

2.2 Recommended Dosage

The recommended starting dosage and the highest recommended dosage of ALVESCO are listed in Table 1

Table 1: Recommended Dosages for Adults and Pediatric Patients 12 Years and Older
Previous Therapy | Recommended Starting Dosage | Highest Recommended Dosage
Patients ≥ 12 years who received bronchodilators alone | 80 mcg twice daily | 160 mcg twice daily
Patients ≥ 12 years who received inhaled corticosteroids | 80 mcg twice daily | 320 mcg twice daily
Patients ≥ 12 years who received oral corticosteroids^1 | 320 mcg twice daily | 320 mcg twice daily
^1Prednisone should be reduced gradually, no faster than 2.5 mg/day on a weekly basis, beginning after at least 1 week of therapy with ALVESCO. Patients should be carefully monitored for signs of asthma instability, including monitoring of serial objective measures of airflow, and for signs of adrenal insufficiency during steroid taper and following discontinuation of oral corticosteroid therapy [see Warnings and Precautions (5.1)] .

General Dosing Recommendations

Individual patients will experience a variable time to onset and degree of symptom relief. Maximum benefit may not be achieved for four weeks or longer after initiation. After asthma stability has been achieved, it is desirable to titrate to the lowest effective dosage to reduce the possibility of side effects. For patients who do not respond adequately to the starting dose after 4 weeks of therapy, higher doses may provide additional asthma control. Patients should not exceed the highest recommended dosage per day.

3 DOSAGE FORMS AND STRENGTHS

Inhalation aerosol:

- 80 mcg of ciclesonide per actuation, supplied with a brown plastic actuator with a red dust cap
- 160 mcg of ciclesonide per actuation, supplied with a red plastic actuator with a red dust cap

4 CONTRAINDICATIONS

ALVESCO is contraindicated in:

- the primary treatment of status asthmaticus or other acute episodes of asthma where intensive measures are required.
- patients with known hypersensitivity to ciclesonide or any of the ingredients of ALVESCO. Rare cases of hypersensitivity reactions with manifestations such as angioedema, with swelling of the lips, tongue and pharynx, have been reported.

5 WARNINGS AND PRECAUTIONS

5.1 Oropharyngeal Candidiasis

In clinical trials, the development of localized infections of the mouth and pharynx with Candida albicansoccurred in 32 of 3038 patients treated with ALVESCO. Of the 32 reported cases, 20 occurred in 1394 patients treated with a total daily dose of 320 mcg of ALVESCO or higher. Most cases of Candidainfection were mild to moderate. When such an infection occurs, treat it with appropriate local or systemic (i.e., oral antifungal) therapy and discontinue ALVESCO. Patients should rinse the mouth after inhalation of ALVESCO.

5.2 Acute Asthma Episodes

ALVESCO is not a bronchodilator and is not indicated for rapid relief of bronchospasm or other acute episodes of asthma. Patients should be instructed to contact their physician immediately if episodes of asthma not responsive to their usual doses of bronchodilators occur during the course of treatment with ALVESCO. During such episodes, patients may require therapy with oral corticosteroids.

5.3 Immunosuppression and Risk of Infections

Persons who are using drugs that suppress the immune system are more susceptible to infections than healthy individuals. Chickenpox and measles, for example, can have a more serious or even fatal course in susceptible children or adults using corticosteroids. In such children or adults who have not had these diseases or been properly immunized, particular care should be taken to avoid exposure. How the dose, route, and duration of corticosteroid administration affect the risk of developing a disseminated infection is not known. The safety and effectiveness of ALVESCO have not been established in pediatric patients less than 12 years of age and ALVESCO is not indicated for use in this population. The contribution of the underlying disease and/or prior corticosteroid treatment to the risk is also not known. If exposed to chickenpox, prophylaxis with varicella zoster immune globulin (VZIG) may be indicated. If exposed to measles, prophylaxis with pooled intramuscular immunoglobulin (IG) may be indicated. (See Prescribing Information for VZIG and IG.) If chickenpox develops, treatment with antiviral agents may be considered.

Inhaled corticosteroids should be used with caution, if at all, in patients with active or quiescent tuberculosis infection of the respiratory tract; untreated systemic fungal, bacterial, viral, or parasitic infections; or ocular herpes simplex.

5.4 Transferring Patients from Systemic Corticosteroid Therapy

HPA Suppression/Adrenal Insufficiency

Particular care is needed for patients who are transferred from systemically active corticosteroids to ALVESCO because deaths due to adrenal insufficiency have occurred in asthmatic patients during and after transfer from systemic corticosteroids to less systemically-available inhaled corticosteroids. After withdrawal from systemic corticosteroids, a number of months are required for recovery of hypothalamic-pituitary-adrenal (HPA) function.

Patients who have been previously maintained on 20 mg or more per day of prednisone (or its equivalent) may be most susceptible, particularly when their systemic corticosteroids have been almost completely withdrawn. During this period of HPA suppression, patients may exhibit signs and symptoms of adrenal insufficiency when exposed to trauma, surgery, or infection (particularly gastroenteritis) or other conditions associated with severe electrolyte loss. Although ALVESCO may provide control of asthma symptoms during these episodes, in recommended doses it supplies less than normal physiological amounts of corticosteroid systemically and does NOT provide the mineralocorticoid activity that is necessary for coping with these emergencies.

During periods of stress or a severe asthma attack, patients who have been withdrawn from systemic corticosteroids should be instructed to resume oral corticosteroids (in large doses) immediately and to contact their physicians for further instruction. These patients should also be instructed to carry a medical identification card indicating that they may need supplementary systemic corticosteroids during periods of stress or a severe asthma attack.

Patients requiring oral corticosteroids should be weaned slowly from systemic corticosteroid use after transferring to ALVESCO. Prednisone reduction can be accomplished by reducing the daily prednisone dose by 2.5 mg on a weekly basis during ALVESCO therapy [see Dosage and Administration (2)] . Lung function (FEV1or AM PEFR), beta-agonist use, and asthma symptoms should be carefully monitored during withdrawal of oral corticosteroids. In addition to monitoring asthma signs and symptoms, patients should be observed for signs and symptoms of adrenal insufficiency, such as fatigue, lassitude, weakness, nausea and vomiting, and hypotension.

Unmasking of Allergic Conditions Previously Suppressed by Systemic Corticosteroids

Transfer of patients from systemic steroid therapy to ALVESCO may unmask allergic conditions previously suppressed by the systemic steroid therapy, e.g., rhinitis, conjunctivitis, eczema, arthritis, and eosinophilic conditions.

Corticosteroid Withdrawal Symptoms

During withdrawal from oral steroids, some patients may experience symptoms of systemically active steroid withdrawal, e.g., joint and/or muscular pain, lassitude, and depression, despite maintenance or even improvement of respiratory function.

5.5 Hypercorticism and Adrenal Suppression

ALVESCO will often help control asthma symptoms with less suppression of HPA function than therapeutically similar oral doses of prednisone. Since individual sensitivity to effects on cortisol production exists, physicians should consider this information when prescribing ALVESCO. Particular care should be taken in observing patients postoperatively or during periods of stress for evidence of inadequate adrenal response.

Hypercorticism and adrenal suppression may occur when corticosteroids, including ALVESCO, are used at higher-than-recommended dosages [see Dosage and Administration (2)] or patients at risk for such effects.

5.6 Reduction in Bone Mineral Density

Decreases in bone mineral density (BMD) have been observed with long-term administration of products containing inhaled corticosteroids. The clinical significance of small changes in BMD with regard to long-term outcomes is unknown. Patients with major risk factors for decreased bone mineral content, such as prolonged immobilization, family history of osteoporosis, or chronic use of drugs that can reduce bone mass (e.g., anticonvulsants and oral corticosteroids) should be monitored and treated with established standards of care.

5.7 Effect on Growth

Orally inhaled corticosteroids, including ALVESCO, may cause a reduction in growth velocity when administered to pediatric patients. The safety and effectiveness of ALVESCO have not been established in pediatric patients less than 12 years of age and ALVESCO is not indicated for use in this population. Monitor the growth of pediatric patients receiving ALVESCO routinely (e.g., via stadiometry). To minimize the systemic effects of orally inhaled corticosteroids, including ALVESCO, titrate each patient’s dose to the lowest dosage that effectively controls his/her symptoms [see Use in Specific Populations (8.4)] .

5.8 Glaucoma and Cataracts

Glaucoma, increased intraocular pressure, and cataracts have been reported following the administration of inhaled corticosteroids including ALVESCO. Therefore, close monitoring is warranted in patients with a change in vision or with a history of increased intraocular pressure, glaucoma, and/or cataracts.

In a comparator control study of one-year treatment duration, 743 patients 18 years of age and older (mean age 43.1 years) with moderate persistent asthma were treated with ALVESCO 320 mcg twice daily and 742 were treated with a labeled dose of a comparator-inhaled corticosteroid appropriate for the patient population. Patients had an ophthalmology examination that included visual acuity, intraocular pressure measurement, and a slit lamp examination at baseline, 4, 8 and 12 months. Lens opacities were graded using the Lens Opacification System III. After 52 weeks, CLASS I effects (minimally detected changes) were recorded in 36.1% of the ALVESCO-treated patients and in 38.4% of patients treated with the comparator-inhaled corticosteroid. The more severe CLASS III effects were recorded in 8.1% of the ALVESCO-treated patients and 9.2% of patients treated with the comparator-inhaled corticosteroid. Of those patients having a CLASS III effect, the incidence of posterior sub-capsular opacities was 0.9% and 0.5% in the ALVESCO- and comparator-treated patients, respectively.

5.9 Paradoxical Bronchospasm

As with other inhaled asthma medications, bronchospasm, with an immediate increase in wheezing, may occur after dosing. If bronchospasm occurs following dosing with ALVESCO, it should be treated immediately with a fast-acting inhaled bronchodilator. Treatment with ALVESCO should be discontinued and alternative treatment should be instituted.

6 ADVERSE REACTIONS

The following clinically significant adverse reactions are described elsewhere in the labeling:

- Oropharyngeal Candidiasis [see Warnings and Precautions (5.1)]
- Immunosuppression and Risk of Infections [see Warnings and Precautions (5.3)]
- Hypercorticism and Adrenal Suppression [see Warnings and Precautions (5.5)]
- Reduction in Bone Mineral Density [see Warnings and Precautions (5.6)]
- Growth Effects [see Warnings and Precautions (5.7)]
- Glaucoma and Cataracts [see Warnings and Precautions (5.8)]

6.1 Clinical Trial Experience

The safety data described below for adult and pediatric patients 12 years of age and older reflect exposure to ALVESCO in doses ranging from 80 mcg to 640 mcg twice daily in five double-blind placebo-controlled clinical trials. Studies with once daily dosing are omitted from the safety database because the doses studied once daily are lower than the highest recommended twice daily doses. The five studies were of 12 to 16 weeks treatment duration, one of which included a safety extension follow-up of one year. In the 12 to 16 week treatment studies, 720 patients (298 males and 422 females) aged 12 years and older were exposed to ALVESCO. In the long-term safety trial, 197 patients (82 males and 115 females) with severe persistent asthma from one of the 12-week trials were re-randomized and treated for up to one year with ALVESCO 320 mcg twice daily.

Because clinical trials are conducted under widely varying conditions, adverse reaction rates observed in the clinical trials of a drug cannot be directly compared to rates in the clinical trials of another drug and may not reflect the rates observed in practice.

Adults and Pediatric Patients 12 Years of Age and Older

Four of the five trials included a total of 624 patients ages 12 years and older (359 females and 265 males) with asthma of varying severity who were treated with ALVESCO 80 mcg, 160 mcg, or 320 mcg twice daily for 12 to 16 weeks. These studies included patients previously using either controller therapy (predominantly inhaled corticosteroids) or reliever therapy (bronchodilator therapy alone). In these trials, the mean age was 39.1 years, and the majority of the patients (79.0%) were Caucasian. In these trials, 52.3%, 59.8% and 54.1% of the patients in the ALVESCO 80 mcg, 160 mcg, and 320 mcg treatment groups, respectively, had at least one adverse event compared to 58.0% in the placebo group.

Table 2includes adverse reactions for the recommended doses of ALVESCO that occurred at an incidence of ≥ 3% in any of the ALVESCO groups and which were more frequent with ALVESCO compared to placebo.

Table 2: Adverse Reactions with ≥ 3% Incidence Reported in Patients ≥ 12 Years of Age with ALVESCO in US Placebo-Controlled Clinical Trials in Patients Previously on Bronchodilators and/or Inhaled Corticosteroids
Adverse Reaction | Placebo (N=507) % | ALVESCO
Adverse Reaction | Placebo (N=507) % | 80 mcg BID (N=325) % | 160 mcg BID (N=127) % | 320 mcg BID (N=172) %
Headache | 7.3 | 4.9 | 11.0 | 8.7
Nasopharyngitis | 7.5 | 10.5 | 8.7 | 7.0
Sinusitis | 3.0 | 3.1 | 5.5 | 5.2
Pharyngolaryngeal pain | 4.3 | 4.3 | 2.4 | 4.7
Upper respiratory Inf. | 6.5 | 7.1 | 8.7 | 4.1
Arthralgia | 1.0 | 0.9 | 2.4 | 3.5
Nasal congestion | 1.6 | 1.8 | 5.5 | 2.9
Pain in extremity | 1.0 | 0.3 | 3.1 | 2.3
Back pain | 2.0 | 0.6 | 3.1 | 1.2

The following adverse reactions occurred in these clinical trials using ALVESCO with an incidence of less than 1% and occurred at a greater incidence with ALVESCO than with placebo.

Infections and Infestations: Oral candidiasis

Respiratory Disorders: Cough

Gastrointestinal Disorders: Dry mouth, nausea

General Disorders and Administrative Site Conditions: Chest discomfort

Respiratory, Thoracic, and Mediastinal Disorders: Dysphonia, dry throat

The fifth study was a 12-week clinical trial in asthma patients 12 years of age and older who previously required oral corticosteroids (average daily dose of oral prednisone of 12 mg/day), in which the effects of ALVESCO 320 mcg twice daily (n = 47) and 640 mcg twice daily (n = 49) were compared with placebo (n = 45) for the frequency of reported adverse reactions. The following adverse reactions occurred at an incidence of ≥ 3% in the ALVESCO-treated patients and were more frequent compared to placebo: sinusitis, hoarseness, oral candidiasis, influenza, pneumonia, nasopharyngitis, arthralgia, back pain, musculoskeletal chest pain, headache, urticaria, dizziness, gastroenteritis, face edema, fatigue, and conjunctivitis.

Long-Term Clinical Trials Experience

A total of 197 patients 12 years of age and older (82 males and 115 females) from one of the 12-week treatment placebo-controlled studies were re-randomized to ciclesonide 320 mcg twice daily and followed for one year. The safety profile from the one-year follow-up was similar to that seen in the 12- and 16-week treatment studies.

6.2 Post-marketing Experience

In addition to adverse reactions identified from clinical trials, the following adverse reactions have been identified during worldwide post-marketing use of ciclesonide oral inhalation. Because these reactions are reported voluntarily from a population of uncertain size, it is not always possible to reliably estimate their frequency or establish a causal relationship to drug exposure.

Immune System Disorders: Immediate or delayed hypersensitivity reactions such as angioedema with swelling of the lips, tongue and pharynx.

7 DRUG INTERACTIONS

In clinical studies, concurrent administration of ciclesonide and other drugs commonly used in the treatment of asthma (albuterol, formoterol) had no effect on pharmacokinetics of des-ciclesonide [see Clinical Pharmacology (12.3)] .

In vitrostudies and clinical pharmacology studies suggested that des-ciclesonide has no potential for metabolic drug interactions or protein binding-based drug interactions [see Clinical Pharmacology (12.3)] .

In a drug interaction study, co-administration of orally inhaled ciclesonide and oral ketoconazole, a potent inhibitor of cytochrome P450 3A4, increased the exposure (AUC) of des-ciclesonide by approximately 3.6-fold at steady state, while levels of ciclesonide remained unchanged.

8 USE IN SPECIFIC POPULATIONS

8.1 Pregnancy

Risk Summary

There are no available data on ALVESCO use in pregnant women to assess a drug associated risk of major birth defects, miscarriage, or adverse maternal or fetal outcomes. There is low systemic exposure following ALVESCO oral inhalation administration at the recommended dose [see Clinical Pharmacology (12.3)] .

In animal reproduction studies, ciclesonide administered by the oral route to pregnant rats during the period of organogenesis did not cause any evidence of fetal harm at doses up to 15 times the maximum recommended human daily oral inhalation dose (MRHDOID) of 640 mcg/day. Teratogenicity, characteristic of corticosteroids, decreased body weight and/or skeletal variations were observed in rabbit fetuses following administration of ciclesonide to pregnant rabbits by the subcutaneous route during the period of organogenesis at doses 0.15 times the MRHDOID and higher on a mcg/m^2basis (see Data). No evidence of fetal harm was observed in rabbits at doses of 0.03 times the MRHDOID.

All pregnancies have a background risk of birth defect, loss, or other adverse outcomes. The estimated background risk of major birth defects and miscarriage for the indicated population is unknown. In the United States general population, the estimated background risk of major birth defects and miscarriage in clinically recognized pregnancies is 2% to 4% and 15% to 20%, respectively.

Clinical Considerations

Disease-Associated Maternal and/or Embryo/Fetal Risk

In women with poorly or moderately controlled asthma, there is an increased risk of several perinatal outcomes such as pre‑eclampsia in the mother and prematurity, low birth weight, and small for gestational age in the neonate. Pregnant women with asthma should be closely monitored and medication adjusted as necessary to maintain optimal asthma control.

Data

Animal Data

In an embryo-fetal development study in pregnant rats dosed by the oral route during the period of organogenesis from gestation days 6 to 15, ciclesonide did not cause any evidence of fetal harm at doses up to approximately 15 times the MRHDOID in adults (on a mcg/m^2basis with maternal oral dose up to 900 mcg/kg/day). Maternal toxicity, as evidenced by decreased body weight gain, was observed at approximately 15 times the MRHDOID in adults (on a mcg/m^2basis at a maternal dose of 900 mcg/kg/day); however, no adverse effects were observed at doses 5 times the MRHDOID and lower (on a mcg/m^2basis with maternal oral doses of 300 mcg/kg/day and lower).

In two embryo-fetal development studies in pregnant rabbits dosed by the subcutaneous route during the period of organogenesis from gestation days 6 to 18, ciclesonide caused acampsia (flexures of legs) in fetuses at doses 0.15 times the MRHDOID and higher (on a mcg/m^2basis with maternal oral doses of 5 mcg/kg/day and higher), decreased body weight, cleft palate, enlarged fontanelle, parchment-like skin, and incomplete ossification of bones in fetuses at doses 0.76 times the MRHDOID (on a mcg/m^2basis with a maternal subcutaneous dose of 25 mcg/kg/day), and embryo-fetal death at doses 3 times the MRHDOID and higher (on a mcg/m^2basis with maternal subcutaneous doses of 100 mcg/kg/day and higher). No evidence of fetal harm was observed at a dose 0.03 times the MRHDOID in adults (on a mcg/m^2basis at a maternal subcutaneous dose of 1 mcg/kg/day). Maternal toxicity was observed at doses 3 times the MRHDOID in adults (on a mcg/m^2basis with maternal subcutaneous doses of 100 mcg/kg/day and lower); however, no evidence of toxicity was observed at doses 0.76 times the MRHDOID and lower (on a mcg/m^2basis with maternal subcutaneous doses of 25 mcg/kg/day and lower).

In a prenatal and postnatal development study in pregnant rats dosed by the oral route from gestation day 6 to lactation day 20, ciclesonide produced no adverse developmental effects on offspring at doses up to approximately 15 times the MRHDOID (on a mcg/m^2basis at maternal oral doses up to 900 mcg/kg/day).

8.2 Lactation

Risk Summary

There are no data on the presence of ciclesonide or its metabolite in human milk, the effects on the breastfed infant, or the effects on milk production. It is not known whether oral inhalation administration of ciclesonide at the recommended dose could result in sufficient systemic absorption to produce detectable quantities in human milk [see Clinical Pharmacology (12.3)] . The developmental and health benefits of breastfeeding should be considered along with the mother’s clinical need for ALVESCO, and any potential adverse effects on the breastfed infant from ALVESCO, or from the underlying maternal condition.

Clinical Considerations

The molecular weight of the prodrug ciclesonide (approximately 541 g/mol) is small enough to be excreted into breast milk; however, its high plasma protein binding affinity and very short half-life suggests that minimal amounts will be present within the milk. Conversely, the half-life of the active metabolite des-ciclesonide (approximately 471 g/mol) suggests that exposure to the nursing infant will be greater than that of the prodrug ciclesonide. Although ciclesonide and des-ciclesonide have negligible oral bioavailability (both less than 1% for each) due to low gastrointestinal absorption and high first-pass metabolism, the relative anti‑inflammatory activity of des-ciclesonide is 120 times greater than that of the ciclesonide and 12 times greater than that of dexamethasone [see Clinical Pharmacology (12.1)] . The effects of this exposure on a nursing infant are unknown, however, like all corticosteroids, suppression of the HPA function is a potential complication.

Data

Animal Data

A study with^14C-ciclesonide showed milk exposure of rat pups to 0.006% of the dose secreted in milk.

8.4 Pediatric Use

The safety and effectiveness of ALVESCO for the maintenance treatment of asthma as prophylactic therapy have been established in pediatric patients aged 12 years and older. Use of ALVESCO for this indication is supported by evidence from randomized, double-blind, placebo-controlled, parallel-group clinical trials in adult and pediatric patients 12 years of age and older with mild persistent to severe persistent asthma [see Clinical Studies (14)] .

The safety and effectiveness of ALVESCO have not been established in pediatric patients younger than 12 years of age.

Pediatric Patients 4 to 11 years of age

Effectiveness was not demonstrated in two randomized, double-blind, placebo-controlled studies that were conducted to evaluate the efficacy of ALVESCO 40, 80, or 160 mcg administered once daily for 12 weeks in patients 4 to 11 years of age with asthma. These studies included 1018 patients previously using either controller therapy (predominately inhaled corticosteroids) or reliever therapy (bronchodilator therapy alone). The patients had a mean baseline percent predicted FEV1of 68%. The primary efficacy endpoint was morning pre-dose FEV1. Other measures of efficacy included AM PEF, asthma symptoms, and rescue albuterol use. The studies showed inconsistent results and did not establish the efficacy of ALVESCO in patients 4 to 11 years of age.

Pediatric Patients 2 to 6 years of age

Effectiveness was not demonstrated in one randomized, double-blind, placebo-controlled study that was conducted to evaluate the efficacy of ALVESCO 40, 80, and 160 mcg administered once daily for 24 weeks in 992 patients 2 to 6 years of age with persistent asthma. The primary efficacy endpoint was time to the first severe asthma exacerbation [defined as worsening of asthma which required treatment with systemic (including oral) steroids or any other asthma medication besides treatment medication and rescue medication] or lack of improvement, whichever occurred first. No statistically significant differences were observed for the individual comparisons of ALVESCO 40, 80, and 160 mcg to placebo. Results from this study did not establish efficacy of ALVESCO in patients 2 to 6 years of age.

Studies in children under 2 years of age have not been conducted given the lack of efficacy observed in patients 2 to 11 years of age.

Effect on Growth

Controlled clinical studies have shown that orally inhaled corticosteroids may cause a reduction in growth velocity in pediatric patients. In these studies, the mean reduction in growth velocity was approximately one centimeter per year (range 0.3 to 1.8 cm per year) and appears to be related to dose and duration of exposure. This effect has been observed in the absence of laboratory evidence of hypothalamic-pituitary-adrenal (HPA) axis suppression, suggesting that growth velocity is a more sensitive indicator of systemic corticosteroid exposure in pediatric patients than some commonly used tests of HPA axis function. The long-term effects of this reduction in growth velocity associated with orally inhaled corticosteroids, including the impact on final adult height, are unknown. The potential for "catch up" growth following discontinuation of treatment with orally inhaled corticosteroids has not been adequately studied. The growth of pediatric patients receiving orally inhaled corticosteroids, including ALVESCO, should be monitored routinely (e.g., via stadiometry).

A 52-week, multi-center, double-blind, randomized, placebo-controlled, parallel-group study was conducted to assess the effect of orally inhaled ciclesonide on growth rate in 609 pediatric patients with mild persistent asthma, aged 5 to 8.5 years. Treatment groups included orally inhaled ciclesonide 40 mcg or 160 mcg or placebo given once daily. Growth was measured by stadiometer height during the baseline, treatment and follow-up periods. The primary comparison was the difference in growth rates between ciclesonide 40 mcg and 160 mcg and placebo groups. Conclusions cannot be drawn from this study because compliance could not be assured. There was no difference in efficacy measures between the placebo and the ALVESCO groups. Ciclesonide blood levels were also not measured during the one-year treatment period.

The potential growth effects of prolonged treatment with orally inhaled corticosteroids should be weighed against clinical benefits obtained and the availability of safe and effective noncorticosteroid treatment alternatives. To minimize the systemic effects of orally inhaled corticosteroids, including ALVESCO, each patient should be titrated to his/her lowest effective dose.

8.5 Geriatric Use

Clinical studies of ALVESCO did not include sufficient numbers of patients aged 65 years and older to determine whether they respond differently than younger patients. Other reported clinical experience has not identified differences in responses between the elderly and younger patients. In general, dose selection for an elderly patient should be cautious, usually starting at the low end of the dosing range reflecting the greater frequency of decreased hepatic, renal, or cardiac function and of concomitant disease or other drug therapy.

10 OVERDOSAGE

Chronic overdosage may result in signs/symptoms of hypercorticism [see Warnings and Precautions (5.5)] .

11 DESCRIPTION

The active component of ALVESCO 80 mcg, and ALVESCO 160 mcg is ciclesonide, a non-halogenated glucocorticoid having the chemical name pregna-1,4-diene-3,20-dione, 16,17-[[(R)-cyclohexylmethylene]bis(oxy)]-11-hydroxy-21-(2-methyl-1-oxopropoxy)-,(11β,16α). The empirical formula is C32H44O7and its molecular weight is 540.7. Its structural formula is as follows:

Ciclesonide is a white to yellow-white powder. It is soluble in dehydrated alcohol, acetone, dichloromethane, and chloroform.

ALVESCO 80 mcg and ALVESCO 160 mcg are pressurized, metered-dose aerosol units fitted with a dose indicator. ALVESCO is intended for oral inhalation only. Each unit contains a solution of ciclesonide in propellant HFA-134a (1,1,1,2 tetrafluoroethane) and ethanol. After priming, ALVESCO 80 mcg delivers 100 mcg from the valve and 80 mcg of ciclesonide from the actuator. ALVESCO 160 mcg delivers 200 mcg from the valve and 160 mcg of ciclesonide from the actuator. This product delivers 50 microliters (59.3 milligrams) of solution as a fine particle mist from the valve with each actuation. The actual amount of drug delivered to the lung may depend on patient factors, such as the coordination between the actuation of the device and inspiration through the delivery system. ALVESCO should be “primed” by actuating 3 times prior to using the first dose from a new canister or when the inhaler has not been used for more than 10 days. Avoid spraying in the eyes or face while priming ALVESCO.

12 CLINICAL PHARMACOLOGY

12.1 Mechanism of Action

Ciclesonide is a prodrug that is enzymatically hydrolyzed to a pharmacologically active metabolite, C21-desisobutyryl-ciclesonide (des-ciclesonide or RM1) following oral inhalation. Des-ciclesonide has anti-inflammatory activity with affinity for glucocorticoid receptors that is 120 times greater than the parent compound and 12 times greater than dexamethasone. The clinical significance of these findings is unknown.

The precise mechanisms of corticosteroid action in asthma are unknown. Inflammation is recognized as an important component in the pathogenesis of asthma. Corticosteroids have been shown to have a wide range of inhibitory activities against multiple cell types (e.g., mast cells, eosinophils, basophils, lymphocytes, macrophages, and neutrophils) and mediators (e.g., histamine, eicosanoids, leukotrienes, and cytokines) involved in the asthmatic response. These anti-inflammatory actions of corticosteroids may contribute to their efficacy in asthma. Though effective for the treatment of asthma, corticosteroids do not affect asthma symptoms immediately. Individual patients will experience a variable time to onset and degree of symptom relief. Maximum benefit may not be achieved for four weeks or longer after starting treatment. When corticosteroids are discontinued, asthma stability may persist for several days or longer.

12.2 Pharmacodynamics

The effect of ciclesonide by oral inhalation on the HPA axis was assessed in adults with mild asthma in a 29-day placebo-controlled study. Twenty-four-hour urinary-free cortisol was assessed in a total of 59 adults who were randomized to 320 mcg or 640 mcg ALVESCO, a comparator corticosteroid, or placebo twice daily. At the end of 29 days of treatment, the mean (SE) change from baseline in 24-hr urinary-free cortisol was -8.69 (5.6) mcg/day, -4.01 (5.03) mcg/day, and -8.84 (5.02) mcg/day for the placebo, ALVESCO 640 mcg/day, and ALVESCO 1280 mcg/day, respectively. The difference from placebo for the change from baseline in 24-hr urinary-free cortisol was +4.7 mcg/day [95% CI: -10.58; 19.93] and -0.16 mcg/day [95% CI: -15.20; 14.89] for the 640 mcg/day or 1280 mcg/day treatments, respectively. The effects observed with the comparator corticosteroid validate the sensitivity of the study to assess the effect of ciclesonide on the HPA axis.

12.3 Pharmacokinetics

Absorption: Ciclesonide and des-ciclesonide have negligible oral bioavailability (both are less than 1%) due to low gastrointestinal absorption and high first-pass metabolism. Serum concentrations of ciclesonide and des-ciclesonide were measured and compared following oral inhalation of 1280 mcg ALVESCO and intravenous administration of 800 mcg ciclesonide. The absolute bioavailability of ciclesonide was 22% and the relative systemic exposure of des-ciclesonide was 63%. The mean Cmaxfor des-ciclesonide was 1.02 ng/mL (range 0.6-1.5 ng/mL) in asthmatic patients following a single dose of 1280 mcg by oral inhalation. The mean Cmax(0.369 ng/mL) and AUC0-∞(2.18 ng·hr/mL) of des‑ciclesonide following multiple dose administration of ciclesonide 320 mcg once daily increased up to 26% compared to single dose administration.

Distribution: Following intravenous administration of 800 mcg of ciclesonide, the volumes of distribution of ciclesonide and des-ciclesonide was approximately 2.9 L/kg and 12.1 L/kg, respectively. The percentage of ciclesonide and des-ciclesonide bound to human plasma proteins averaged ≥ 99% each, with ≤ 1% of unbound drug detected in the systemic circulation. Des-ciclesonide is not significantly bound to human transcortin.

Elimination: Following intravenous administration of 800 mcg of ciclesonide, the clearances of ciclesonide and des-ciclesonide were high (approximately 152 L/L/hr and 228 L/L/hr, respectively).^14C-labeled ciclesonide was predominantly excreted via the feces after intravenous administration (66%) indicating that excretion through bile is the major route of elimination. Approximately 20% or less of des-ciclesonide was excreted in the urine. The mean half-life of ciclesonide and des-ciclesonide was 0.71 hours and 6 to 7 hours, respectively. Tmaxof des-ciclesonide occurs at 1.04 hours following inhalation of ciclesonide.

Metabolism: Ciclesonide is hydrolyzed to a biologically active metabolite, des-ciclesonide, by esterases. Des-ciclesonide undergoes further metabolism in the liver to additional metabolites mainly by the cytochrome P450 (CYP) 3A4 isozyme and to a lesser extent by CYP 2D6. The full range of potentially active metabolites of ciclesonide has not been characterized. After intravenous administration of^14C-ciclesonide, 19.3% of the resulting radioactivity in the plasma is accounted for by ciclesonide or des-ciclesonide; the remainder may be a result of other, as yet, unidentified multiple metabolites.

Specific Populations: Population pharmacokinetic analysis showed that characteristics of des-ciclesonide after oral inhalation of ciclesonide were not appreciably influenced by a variety of subject characteristics such as body weight, age, race, and gender.

Patients with Renal Impairment: Studies in renally-impaired patients were not conducted since renal excretion of des-ciclesonide is a minor route of elimination (≤ 20%).

Patients with Hepatic Impairment: Compared to healthy subjects, the systemic exposure of des-ciclesonide (Cmaxand AUC) in patients with moderate to severe liver impairment increased in the range of 1.4 to 2.7 fold after 1280 mcg ex-actuator ciclesonide by oral inhalation. Dose adjustment in patients with liver impairment is not necessary.

Drug Interaction Studies: In a drug interaction study, co-administration of orally inhaled ciclesonide and oral ketoconazole, a potent inhibitor of cytochrome P450 3A4, increased the exposure (AUC) of ciclesonide active metabolite, des-ciclesonide, by approximately 3.6-fold at steady state, while levels of ciclesonide remained unchanged [see Drug Interactions (7)] .

In another single-dose drug interaction study, co-administration of orally inhaled ciclesonide and oral erythromycin, an inhibitor of cytochrome P450 3A4, had no effect on the pharmacokinetics of either ciclesonide and the active metabolite, des-ciclesonide, or erythromycin.

Based on in vitrostudies in human liver microsomes, des-ciclesonide had no significant potential to inhibit or induce the metabolism of other drugs metabolized by CYP450 enzymes. The inhibitory potential of ciclesonide on CYP450 isoenzymes has not been studied. Based on in vitrohuman hepatocyte studies, ciclesonide and des-ciclesonide had no potential to induce major CYP450 isozymes.

In vitrostudies demonstrated that the plasma protein binding of des-ciclesonide was not affected by warfarin or salicylic acid, indicating no potential for protein binding-based drug interactions.

In a population pharmacokinetic analysis including 98 subjects, co-administration of ALVESCO and albuterol had no effect on the pharmacokinetics of des-ciclesonide.

Concomitant administration of ALVESCO (640 mcg) and formoterol (24 mcg) did not change the pharmacokinetics of either des-ciclesonide or formoterol.

13 NONCLINICAL TOXICOLOGY

13.1 Carcinogenesis, Mutagenesis, Impairment of Fertility

Two-year carcinogenicity studies in B6C3F1 mice and Wistar rats were conducted to assess the carcinogenic potential of ciclesonide. Ciclesonide demonstrated no tumorigenic potential in a study with mice that received oral doses up to 900 mcg/kg/day (approximately 7 times the MRHDOID in adults and pediatric patients ≥ 12 years of age on a mcg/m^2basis) and a study with rats that received inhalation doses up to 193 mcg/kg/day (approximately 3 times the MRHDOID in adults and pediatric patients ≥ 12 years of age on a mcg/m^2basis).

Ciclesonide was not mutagenic in an Ames test or in the Chinese hamster lung V79 cell/hypoxanthine-guanine phosphoribosyl transferase (HGPRT) forward mutation assay and was not clastogenic in a human lymphocyte chromosomal aberration assay or in an in vitromicronucleus test. However, ciclesonide was clastogenic in an in vivomouse micronucleus test. The concurrent reference corticosteroid (dexamethasone) in this study showed similar findings.

Fertility and reproductive performance were unaffected in male and female rats dosed by the oral route up to 900 mcg/kg/day (approximately 15 times the MRHDOID in adults based on mcg/m^2).

14 CLINICAL STUDIES

14.1 Asthma

Adults and Pediatric Patients 12 Years of Age and Older

The efficacy of ALVESCO was evaluated in six randomized, double-blind, placebo-controlled, parallel-group clinical trials in adult and pediatric patients 12 years of age and older with mild persistent to severe persistent asthma. The six trials included two trials in which patients were treated with ALVESCO administered once daily for 12 weeks, two trials in which patients were treated with ALVESCO twice daily for 12 weeks, and two trials in which patients were treated with ALVESCO using once daily and twice daily dosing regimens for 12 or 16 weeks. These trials included a total of 2843 patients (1167 males and 1676 females) of whom 296 were pediatric patients 12 to 17 years of age. The primary efficacy endpoint in four of the six trials was the mean change from baseline in pre-dose FEV1at endpoint (last observation). FEV1was measured prior to the morning dose of study medication (at the end of the 24-hour dosing interval for once daily administration, and at the end of the 12-hour dosing interval for twice daily administration). In one of the six trials, the primary endpoint was the change from baseline in the average of the pre-dose FEV1at Weeks 12 and 16, and in another trial, reduction of oral corticosteroid use was the primary efficacy endpoint. Additional efficacy variables were asthma symptoms, use of albuterol for rescue, AM PEF, nighttime awakenings, and withdrawal due to asthma worsening.

The two once daily dosing trials were identically designed and were conducted to evaluate the efficacy of ALVESCO 80, 160, and 320 mcg given once daily in the morning for 12 weeks in patients with mild to moderate asthma maintained on inhaled bronchodilators and/or corticosteroids. The results of these trials, along with other trials that explored twice daily dosing, indicate that once daily dosing is not the optimum dosing regimen for ALVESCO.

Four trials were designed to evaluate the efficacy of ALVESCO administered twice daily in patients with asthma who were previously maintained on bronchodilators alone, patients who were previously maintained on inhaled corticosteroids, and patients who were previously maintained on oral corticosteroids.

Patients Previously Maintained on Bronchodilators Alone

The efficacy of ALVESCO was studied in a randomized, double-blind, placebo-controlled trial in 691 patients with mild-to-moderate persistent asthma (mean baseline percent predicted FEV1of 72%) previously using reliever therapy (bronchodilator therapy alone). In this trial, patients were treated with ALVESCO 160 mcg once daily in the morning for 16 weeks, ALVESCO 80 mcg twice daily for 16 weeks, or ALVESCO 80 mcg twice daily for 4 weeks followed by ALVESCO 160 mcg once daily in the morning for 12 weeks or placebo for 16 weeks. Compared to placebo, all ALVESCO doses showed statistically significant improvement at Week 16 in AM pre-dose FEV1. However, the increase in AM pre-dose FEV1in the patients treated with ALVESCO 80 mcg twice daily was significantly greater than that observed in patients treated with ALVESCO 160 mcg administered once daily. Compared to placebo, increases in AM pre-dose FEV1were 0.12 L or 5.0% for ALVESCO 160 mcg once daily, 0.24 L or 10.4% for ALVESCO 80 mcg twice daily, 0.13 L or 5.0% for ALVESCO 80 mcg twice daily for 4 weeks followed by ALVESCO 160 mcg once daily. Other measures of asthma control, AM PEF, and need for rescue albuterol also improved in all the ALVESCO treatment groups compared to placebo but the improvement was greatest with the ALVESCO 80 mcg twice daily treatment arm. Discontinuations from the study for lack of efficacy were lower in the ALVESCO treatment groups compared to placebo. Fewer patients receiving ALVESCO experienced asthma worsening than did patients receiving placebo. The AM pre-dose FEV1results are shown in Figure 1below.

Patients Previously Maintained on Inhaled Corticosteroids

The efficacy of ALVESCO in asthma patients previously maintained on inhaled corticosteroids was evaluated in two randomized, double-blind, placebo-controlled trials of 12-weeks treatment duration. In one trial, asthmatic patients with mild to moderate persistent asthma (mean baseline percent predicted FEV1of 79%), previously maintained on controller therapy (predominantly inhaled corticosteroids) were treated with ALVESCO 160 mcg once daily in the morning, ALVESCO 80 mcg twice daily or placebo.

The AM pre-dose FEV1results are shown in Figure 2below.

Statistically significantly more increases in AM pre-dose FEV1compared to placebo were seen at 12 weeks for ALVESCO 160 mcg once daily (0.14 L or 5.7%) and ALVESCO 80 mcg twice daily (0.19 L or 7.5%). Asthma symptoms scores, AM PEF, and decreased need for rescue albuterol remained relatively stable in the ALVESCO treatment groups compared to slight worsening in the placebo. Compared to placebo, fewer patients receiving ALVESCO experienced worsening of asthma.

In the other trial, 257 patients with moderate to severe persistent asthma (mean baseline percent predicted FEV1of 54%) were treated with ALVESCO 160 or 320 mcg twice daily for 12 weeks. The AM pre-dose FEV1results are shown in Figure 3below.

Compared to placebo, both ALVESCO doses showed statistically significantly more improvement in pre-dose FEV1(0.11 L or 8.6% and 0.18 L or 11.8%). Other measures of asthma control, AM PEF, symptoms, and need for rescue albuterol also showed improvement compared to placebo. Compared to placebo, fewer patients treated with ALVESCO experienced worsening of asthma.

Patients treated with ALVESCO were also less likely to discontinue study participation due to asthma deterioration.

Patients Previously Maintained on Oral Corticosteroids

In a 12-week double-blind clinical trial, 140 patients with severe persistent asthma (mean FEV1at baseline 53% predicted) who had failed prior efforts to eliminate oral prednisone use and had established their lowest effective prednisone dose were randomized to ALVESCO given by oral inhalation at doses of 320 or 640 mcg twice daily or placebo. The average prednisone dose at baseline was approximately 12 mg/day. Compared to patients on placebo whose prednisone requirements increased by 4%, those treated with ALVESCO 320 mcg and 640 mcg twice daily significantly reduced their prednisone requirements by 47% and 62%, respectively. At the same time, patients on ALVESCO maintained asthma control as reflected by lung function, symptoms, and need for rescue albuterol. A significantly larger percentage of patients on ALVESCO were able to reduce oral prednisone use by 50% or more as compared to placebo (64% and 77% of the patients treated with 320 mcg and 640 mcg, respectively twice daily as compared with 33% of patients on placebo). There was no statistically significant difference observed with ALVESCO 640 mcg twice daily compared to ALVESCO 320 mcg twice daily.

16 HOW SUPPLIED/STORAGE AND HANDLING

ALVESCO is available in the following strengths and canister presentations.

Micrograms per Actuation | Number of Actuations per Canister | Canister Weight | Canister per Box | NDC Number
ALVESCO 80 mcg | 60 | 6.1 g | 1 | 70515-711-01
ALVESCO 160 mcg | 60 | 6.1 g | 1 | 70515-712-01
ALVESCO 80 mcg | 30 | 4.7 g | 1 | 70515-711-04
ALVESCO 160 mcg | 30 | 4.7 g | 1 | 70515-712-04
ALVESCO 80 mcg | 60 | 6.1 g | 1 | 70515-711-05
ALVESCO 160 mcg | 60 | 6.1 g | 1 | 70515-712-05

ALVESCO (ciclesonide) 80 mcg inhalation aerosol is supplied with a brown plastic actuator with a red dust cap. Each actuation of the inhaler delivers 80 mcg of ciclesonide from the actuator and contains 60 actuations fill/canister.

ALVESCO 160 (ciclesonide) mcg inhalation aerosol is supplied with a red plastic actuator with a red dust cap. Each actuation of the inhaler delivers 160 mcg of ciclesonide from the actuator and contains 60 actuations fill/canister.

ALVESCO canisters are for use with ALVESCO actuators only. The actuators are fitted with a dose indicator and should not be used with other medications. The correct amount of medication in each actuation cannot be assured from the canister labeled to contain 60 actuations when the dose indicator display window shows zero even though the canister is not completely empty. The canister should be discarded when the dose indicator display window shows zero.

Store at 25°C (77°F). Excursions between 15°C and 30°C (59°F and 86°F) are permitted (see USP). For optimal results, the canister should be at room temperature when used.

Contents under pressure. Do not puncture. Do not use or store near heat or open flame. Exposure to temperatures above 49°C (120°F) may cause bursting. Never throw canister into fire or incinerator.

17 PATIENT COUNSELING INFORMATION

Advise the patient to read the FDA-approved patient labeling (Patient Information and Instructions for Use)

Oropharyngeal Candidiasis

Patients should be advised that localized infections with Candida albicansoccurred in the mouth and pharynx in some patients. If oropharyngeal candidiasis develops, it should be treated with appropriate local or systemic (i.e., oral) antifungal therapy while still continuing with ALVESCO therapy, but at times therapy with the ALVESCO inhaler may need to be temporarily interrupted under close medical supervision. Rinsing the mouth after inhalation is advised [see Warnings and Precautions (5.1)] .

Acute Asthma Episodes

Patients should be advised that ALVESCO is not a bronchodilator and is not intended for use as rescue medication for acute asthma exacerbations. Acute asthma symptoms should be treated with an inhaled, short-acting beta2-agonist such as albuterol. The patient should be instructed to contact their physician immediately if there is deterioration of their asthma [see Warnings and Precautions (5.2)] .

Immunosuppression and Risk of Infections

Patients who are on immunosuppressant doses of corticosteroids should be warned to avoid exposure to chickenpox or measles and, if exposed, to consult their physician without delay. Patients should be informed of potential worsening of existing tuberculosis, fungal, bacterial, viral, or parasitic infections, or ocular herpes simplex [see Warnings and Precautions (5.3)] .

Hypercorticism and Adrenal Suppression

Patients should be advised that ALVESCO may cause systemic corticosteroid effects of hypercorticism and adrenal suppression. Additionally, patients should be instructed that deaths due to adrenal insufficiency have occurred during and after transfer from systemic corticosteroids. Patients should taper slowly from systemic corticosteroids if transferring to ALVESCO [see Warnings and Precautions (5.5)] .

Reduction in Bone Mineral Density

Patients who are at an increased risk for decreased BMD should be advised that the use of corticosteroids may pose an additional risk and should be monitored and where appropriate, be treated for this condition [see Warnings and Precautions (5.6)] .

Effect on Growth

Patients should be informed that orally inhaled corticosteroids, including ALVESCO, may cause a reduction in growth velocity when administered to pediatric patients. Physicians should closely follow the growth of pediatric patients taking corticosteroids by any route [see Warnings and Precautions (5.7)] .

Use Daily for Best Effect

Patients should be advised to use ALVESCO at regular intervals, since its effectiveness depends on regular use. Maximum benefit may not be achieved for four weeks or longer after starting treatment. The patient should not increase the prescribed dosage but should contact their physician if symptoms do not improve or if the condition worsens. Patients should be instructed not to stop ALVESCO use abruptly. Patients should contact their physician immediately if use of ALVESCO is discontinued.

How to Use ALVESCO

Patients should use ALVESCO only with the actuator supplied with the product. When the dose indicator display window shows a red zone, approximately 20 inhalations are left, and a refill is required. Discard the inhaler when the indicator shows zero.

Manufactured for:
Covis Pharma
Zug, 6300 Switzerland
Made in United Kingdom

Patient Information

ALVESCO®[ael-‘ves-ko℧]
(ciclesonide)

Note: For Oral Inhalation Only

Do notuse your ALVESCO near heat or an open flame.

Read this Patient Information leaflet before you start using ALVESCO and each time you get a refill. There may be new information. This information does not take the place of talking with your healthcare provider about your medical condition or your treatment. If you have any questions about ALVESCO, ask your healthcare provider or pharmacist.

What is ALVESCO?

ALVESCO is a prescription medicine used for the control and prevention of asthma in adults and children 12 years of age and older.

ALVESCO contains ciclesonide, which is a man-made (synthetic) corticosteroid. Corticosteroids are natural substances found in the body and reduce inflammation. When you inhale ALVESCO it may help to control and prevent your symptoms of asthma by reducing your airway inflammation.

ALVESCO is not for the relief of acute bronchospasm. ALVESCO is not a bronchodilator and does not treat sudden symptoms of an asthma attack such as wheezing, cough, shortness of breath, and chest pain or tightness. Always have a fast-acting bronchodilator medicine (rescue inhaler) with you to treat sudden symptoms.

It is not known if ALVESCO is safe and effective in children 11 years of age and younger.

Who should not use ALVESCO?

Do not use ALVESCO:

- to treat status asthmaticus or other sudden symptoms of asthma. ALVESCO is not a rescue inhaler and should not be used to give you fast relief from your asthma attack. Always use a rescue inhaler such as albuterol, during a sudden asthma attack.
- if you are allergic to ciclesonide or any of the ingredients in ALVESCO. See the end of this Patient Information leaflet for a complete list of ingredients in ALVESCO.

What should I tell my healthcare provider before using ALVESCO?

Before you use ALVESCO tell your healthcare provider if you:

- have or have had eye problems such as increased ocular pressure, glaucoma, or cataracts.
- have any infections including tuberculosis or ocular herpes simplex.
- have not had or been vaccinated for chicken pox or measles.
- are pregnant or plan to become pregnant. It is not known if ALVESCO will harm your unborn baby. Talk to your healthcare provider if you are pregnant or plan to become pregnant.
- are breastfeeding or plan to breastfeed. It is not known if ALVESCO passes into your breast milk. Talk to your healthcare provider about the best way to feed your baby if you are using ALVESCO.

Tell your healthcare provider about all the medicines you take, including prescription and non-prescription medicines, vitamins and herbal supplements.

Know the medicines you take. Keep a list of them to show your healthcare provider and pharmacist when you get a new medicine.

How should I use ALVESCO?

- Read the Instructions for Use at the end of this leaflet for specific information about the right way to use ALVESCO.
- Use ALVESCO exactly as your healthcare provider tells you to use it. Do not take more of your medicine, or take it more often than your healthcare provider tells you.
- You must use ALVESCO regularly. It may take 4 weeks or longer after you start using ALVESCO for your asthma symptoms to get better. Do not stop using ALVESCO even if you are feeling better, unless your healthcare provider tells you to.
- If your symptoms do not improve or get worse, call your healthcare provider.
- Your healthcare provider may prescribe a rescue inhaler for emergency relief of sudden asthma attacks. Call your healthcare provider if you have:
  - an asthma attack that does not respond to your rescue inhaler or
  - you need more of your rescue inhaler than usual.
- If you use another inhaled medicine, ask your healthcare provider for instructions on how to use it while you use ALVESCO.

What are the possible side effects of ALVESCO?

ALVESCO may cause serious side effects, including:

- Thrush (Candida), a fungal infection of your nose, mouth, or throat.Tell your healthcare provider if you have discomfort or pain in your throat, have hoarseness in your voice or have any redness or white colored patches in your mouth or throat. Rinse your mouth after you use your ALVESCO.
- Immune system problems that may increase your risk of infections.You are more likely to get infections if you take medicines that may weaken your body’s ability to fight infections. Avoid contact with people who have contagious diseases such as chicken pox or measles while you use ALVESCO. Symptoms of an infection may include:
  - fever
  - pain
  - aches
  - chills
  - feeling tired
  - nausea
  - vomiting
- Adrenal insufficiency.Adrenal insufficiency is a condition in which the adrenal glands do not make enough steroid hormones. Your healthcare provider will follow you closely if you take steroids by mouth and are having them decreased (tapered) or you are being switched to ALVESCO. People have died while steroids are being decreased and when people have been switched from steroids by mouth to inhaled steroids like ALVESCO. If you are under stress, such as with surgery, after surgery or trauma, you may need steroids by mouth again.
  Call your healthcare provider right away if you have the following symptoms of adrenal insufficiency:
  - tiredness
  - weakness
  - dizziness
  - nausea that does not go away
  - vomiting that does not go away
- Decreased bone mass (bone mineral density).People who use inhaled steroid medicines for a long time may have an increased risk of decreased bone mass which can affect bone strength. Talk to your healthcare provider about any concerns you may have about bone health.
- Slowed or delayed growth in children.A child’s growth should be checked regularly while using ALVESCO.
- Eye problems such as glaucoma and cataracts.If you have a history of glaucoma or cataracts or have a family history of eye problems, you should have regular eye exams while you use ALVESCO.
- Increased wheezing (bronchospasm)can happen right away after using ALVESCO. Stop using ALVESCO and use an inhaled fast-acting bronchodilator (rescue inhaler) right away.
  Tell your healthcare provider right away so that a new medicine can be prescribed to control your asthma.
  The most common side effects with ALVESCO include:
- headache
- swelling of nose and throat (nasopharyngitis)
- swelling of the sinuses (sinusitis)
- throat pain
- upper respiratory infection
- joint pain (arthralgia)
- nasal congestion
- pain in arms, legs, and back

Tell your healthcare provider about any side effect that bothers you or that does not go away. These are not all of the possible side effects with ALVESCO. For more information, ask your healthcare provider or pharmacist.

Call your healthcare provider for medical advice about side effects. You may report side effects to FDA at 1-800-FDA-1088.

How should I store ALVESCO?

- Store ALVESCO at room temperature between 59°F to 86°F (15°C to 30°C)
- Do notpuncture the ALVESCO canister
- Do notstore the ALVESCO canister near heat or a flame. Temperatures above 120°F (49°C) may cause the canister to burst.
- Do notthrow the ALVESCO canister into a fire or an incinerator.
- Safely throw away medicine that is out of date or no longer needed.
- Keep ALVESCO Aerosol and dry at all times.

Keep ALVESCO and all medicines out of reach of children.

General Information About the Safe and Effective use of ALVESCO

Medicines are sometimes prescribed for purposes other than those listed in a Patient Information leaflet. Do not use ALVESCO for a condition for which it is not prescribed. Do not give ALVESCO to other people, even if they have the same symptoms that you have. It may harm them.

This Patient Information summarizes the most important information about ALVESCO. If you would like more information, talk with your healthcare provider. You can ask your pharmacist or healthcare provider for information about ALVESCO that is written for health professionals.

For more information, go to www.alvesco.us/.

What are the ingredients in ALVESCO?

Active ingredient:ciclesonide

Inactive ingredients:propellant HFA-134a and ethanol

Instructions for Use
ALVESCO®[ael-‘ves- ko℧]
(ciclesonide)

Read this Instructions for Use for ALVESCO before you start using it and each time you get a refill. There may be new information. This leaflet does not take the place of talking to your healthcare provider about your medical condition or treatment.

Note: For Oral Inhalation Only

Do notuse your ALVESCO near heat or an open flame.

The parts of your ALVESCO

ALVESCO comes as a canister that fits into an actuator with a dose indicator. Do notuse the actuator with a canister of medicine from any other inhaler. Do notuse ALVESCO canister with an actuator from any other inhaler. (See Figure A)

Priming your ALVESCO for use

- Remove your ALVESCO from its package.
- Before you use ALVESCO for the first timeor if you have not used your medicine for 10 days in a row, you will need to prime your ALVESCO unit.
- Remove the plastic cap. Look at the dose indicator on top of the inhaler. Make sure that the dose indicator display window pointer is before the “60” inhalation mark before you use your ALVESCO for the first time.
- Hold the actuator upright. Spray 3 times into the air away from the face, by pressing down fully onto the center of the dose indicator button. (See Figure B)

- Check the dose indicator display window after the priming sprays and before the first use to make sure it shows that there are 60 sprays left in your ALVESCO unit. If there are not 60 sprays left in your ALVESCO after the first use priming spray, return it to the pharmacy.
- Make sure the canister is firmly placed in the mouthpiece each time you use your ALVESCO.
- You do not need to shake your ALVESCO unit before you use it.

Using Your ALVESCO

Step 1.Remove the cap from the mouthpiece. (See Figure C)

Step 2.Hold the actuator upright, between your thumb, forefinger, and middle finger with the mouthpiece pointing towards you. (See Figure D)

Step 3.Breathe out as fully as you comfortably can. Close your lips around the mouthpiece, keeping your tongue below it. (See Figure E)

Step 4.

- While breathing in deeply and slowly, press down on the center of the dose indicator with your finger. Press down fully on the canister until it stops moving in the actuator while delivering your dose.
- When you have finished breathing in, hold your breath for about 10 seconds, or for as long as is comfortable.
- Note: It is normal to hear a soft click from the indicator as it counts down during use.

Step 5.

Take your finger completely off the center of the dose indicator and remove the inhaler from your mouth. Breathe out gently. (See Figure F)

Step 6.Replace the cap to keep the mouthpiece clean.

Step 7.Rinse your mouth with water and spit it out. Do notswallow.

Cleaning your ALVESCO unit

- Clean the mouthpiece weekly with a clean dry tissue, both inside and out. (See Figure G)

- Wipe over the front of the small hole where the medicine comes out with a dry, folded tissue. (See Figure H)

- Do not wash or put any part of your ALVESCO unit in water or any other liquids.

How to tell if your ALVESCO canister is empty

- Your ALVESCO unit is fitted with a dose indicator display which shows you how much of your medicine is left after each use.
- Each canister of ALVESCO contains enough medicine for you to spray your medicine 60 times. This does not count the first sprays used for priming.
- The dose indicator display counts down by 10 and will move every tenth time you take a puff (i.e., 60-50-40, etc.).
- The dose indicator display window will turn red when there are only 20 sprays left. This means that you need to replace your inhaler soon.
- When the dose indicator display window reads “0” you should throw away your ALVESCO unit. (See Figure I)

- Although your ALVESCO unit is fitted with a dose indicator display to help determine the number of sprays left, you should keep track of the number of sprays used from each canister of your ALVESCO unit.

This PPI and Instructions for Use has been approved by the U.S. Food and Drug Administration.

Manufactured for:
Covis Pharma
Zug, 6300 Switzerland
Made in United Kingdom

ALVESCO is a registered trademark of Covis Pharma.

©2025 Covis Pharma. All rights reserved.

PRINCIPAL DISPLAY PANEL - 80 mcg Carton

NDC 70515-711-01 Net Contents: 6.1 g

Alvesco®
ciclesonide
Inhalation Aerosol

80 mcg/actuation

60 Metered Actuations

FOR ORAL INHALATION WITH ALVESCO®
INHALATION AEROSOL ACTUATOR ONLY

Rx Only

COVIS

Alvesco®
ciclesonide Inhalation Aerosol

80 mcg/actuation

GTIN: 00370515711013
S/N: XXXXXXXXXXXXXX
EXP: MM/YYYY
LOT: YYXXXX

Pharmacist:Dispense
with Patient’s Instructions
for Use from package
insert inside.

WARNING:Keep out of
reach of children. Avoid
spraying in eyes.

COVIS
Manufactured for:
Covis Pharma
Zug, 6300 Switzerland

Made in the United Kingdom

Each 6.1 g canister of
ALVESCO®Inhalation
Aerosol contains a solution
of ciclesonide in propellant
HFA-134a (1,1,1,2
tetrafluoroethane) and
ethanol. The 80 mcg
strength of ALVESCO®
Inhalation Aerosol delivers
100 mcg from the valve
and 80 mcg of ciclesonide
from the actuator.

Dosage and
Administration:
See package insert for
dosage information.

CONTENTS UNDER
PRESSURE. Do not
puncture.

Do not use or store near
heat or open flame.

Exposure to temperatures
above 49°C (120°F) may
cause bursting. Never
throw canister into fire or
incinerator.

Store at 25°C (77°F);
excursions between
15–30°C (59–86°F) are
permitted [see USP]. For
optimal results, canister
should be at room
temperature when used.

PRINCIPAL DISPLAY PANEL - 160 mcg Carton

NDC 70515-712-01 Net Contents: 6.1 g

Alvesco®
ciclesonide
Inhalation Aerosol

160 mcg/actuation

60 Metered Actuations

FOR ORAL INHALATION WITH ALVESCO®
INHALATION AEROSOL ACTUATOR ONLY

Rx Only

COVIS

Alvesco®
ciclesonide
Inhalation Aerosol

160 mcg/actuation

GTIN: 00370515712010
S/N: XXXXXXXXXXXXXX
EXP: MM/YYYY
LOT: YYXXXX

Pharmacist:Dispense
with Patient’s Instructions
for Use from package
insert inside.

WARNING:Keep out of
reach of children. Avoid
spraying in eyes.

COVIS
Manufactured for:
Covis Pharma
Zug, 6300 Switzerland

Made in the United Kingdom

Each 6.1 g canister of
ALVESCO®Inhalation
Aerosol contains a solution
of ciclesonide in propellant
HFA-134a (1,1,1,2
tetrafluoroethane) and
ethanol. The 160 mcg
strength of ALVESCO®
Inhalation Aerosol delivers
200 mcg from the valve
and 160 mcg of ciclesonide
from the actuator.

Dosage and
Administration:
See package insert for
dosage information.

CONTENTS UNDER
PRESSURE. Do not
puncture.

Do not use or store near
heat or open flame.

Exposure to temperatures
above 49°C (120°F) may
cause bursting. Never
throw canister into fire or
incinerator.

Store at 25°C (77°F);
excursions between
15–30°C (59–86°F) are
permitted [see USP]. For
optimal results, canister
should be at room
temperature when used.